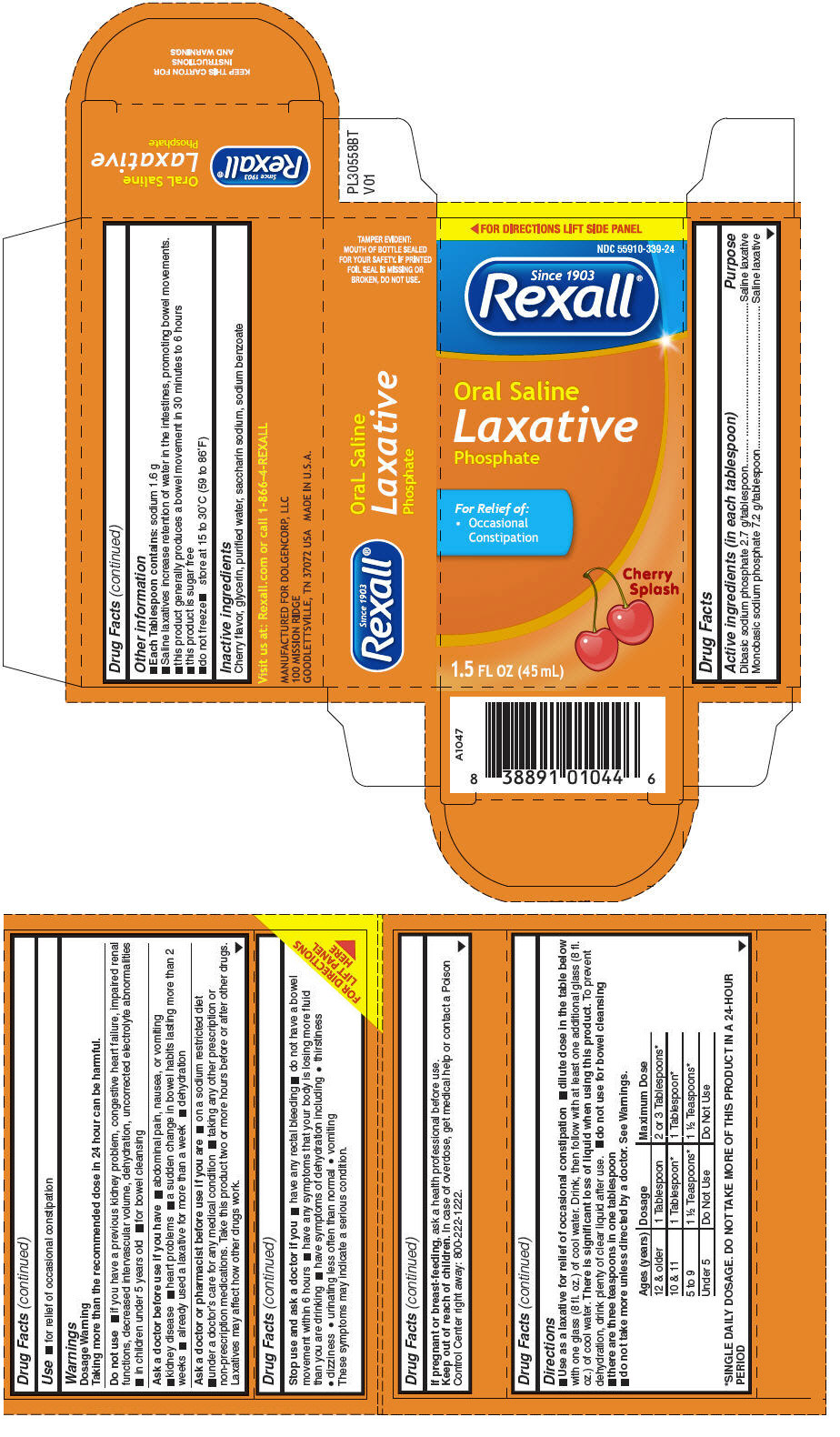 DRUG LABEL: Saline Laxative Cherry 
NDC: 55910-339 | Form: LIQUID
Manufacturer: Dolgencorp Inc.
Category: otc | Type: HUMAN OTC DRUG LABEL
Date: 20170413

ACTIVE INGREDIENTS: Sodium Phosphate, Dibasic 2.7 g/45 mL; Sodium Phosphate, Monobasic, Unspecified Form 7.2 g/45 mL
INACTIVE INGREDIENTS: CHERRY; GLYCERIN; WATER; SACCHARIN SODIUM; SODIUM BENZOATE

Oral Saline Laxative Cherry
Laxative

Drug Facts

ACTIVE INGREDIENT

Active ingredients (in each tablespoon) | Purpose
Dibasic sodium phosphate 2.7 g/tablespoon. | Saline laxative
Monobasic sodium phosphate 7.2 g/tablespoon | Saline laxative

Use

- for relief of occasional constipation

Warnings

Dosage Warning

Taking more than the recommended dose in 24 hour can be harmful.

Do not use

- if you have a previous kidney problem, congestive heart failure, impaired renal functions, decreased intervascular volume, dehydration, uncorrected electrolyte abnormalities
- in children under 5 years old
- for bowel cleansing

Ask a doctor before use if you have

- abdominal pain, nausea, or vomiting
- kidney disease
- heart problems
- a sudden change in bowel habits lasting more than 2 weeks
- already used a laxative for more than a week
- dehydration

Ask a doctor or pharmacist before use if you are

- on a sodium restricted diet
- under a doctor's care for any medical condition
- taking any other prescription or non-prescription medications. Take this product two or more hours before or after other drugs. Laxatives may affect how other drugs work.

Stop use and ask a doctor if you

- have any rectal bleeding
- do not have a bowel movement within 6 hours
- have any symptoms that your body is losing more fluid than you are drinking
- have symptoms of dehydration including
  - thirstiness
  - dizziness
  - urinating less often than normal
  - vomiting

These symptoms may indicate a serious condition.

PREGNANCY OR BREAST FEEDING

If pregnant or breast-feeding, ask a health professional before use.

Keep out of reach of children. In case of overdose, get medical help or contact a Poison Control Center right away: 800-222-1222.

Directions

- Use as a laxative for relief of occasional constipation
- dilute dose in the table below with one glass (8 fl. oz.) of cool water. Drink, then follow with at least one additional glass (8 fl. oz.) of cool water. There is significant loss of liquid when using this product. To prevent dehydration, drink plenty of clear liquid after use.
- do not use for bowel cleansing
- there are three teaspoons in one tablespoon
- do not take more unless directed by a doctor. See Warnings.

Ages (years) | Dosage | Maximum Dose
12 & older | 1 Tablespoon | 2 or 3 Tablespoons [SINGLE DAILY DOSAGE. DO NOT TAKE MORE OF THIS PRODUCT IN A 24-HOUR PERIOD]
10 & 11 | 1 Tablespoon | 1 Tablespoon
5 to 9 | 1 ½ Teaspoons | 1 ½ Teaspoons
Under 5 | Do Not Use | Do Not Use

Other information

- Each Tablespoon contains: sodium 1.6 g
- Saline laxatives increase retention of water in the intestines, promoting bowel movements.
- this product generally produces a bowel movement in 30 minutes to 6 hours
- this product is sugar free
- do not freeze
- store at 15 to 30°C (59 to 86°F)

Inactive ingredients

Cherry flavor, glycerin, purified water, saccharin sodium, sodium benzoate

PRINCIPAL DISPLAY PANEL - 45 mL Bottle Carton

◀ FOR DIRECTIONS LIFT SIDE PANEL

NDC 55910-339-24

Since 1903
Rexall®

Oral Saline
Laxative
Phosphate

For Relief of:

- Occasional
  Constipation

Cherry
Splash

1.5 FL OZ (45 mL)